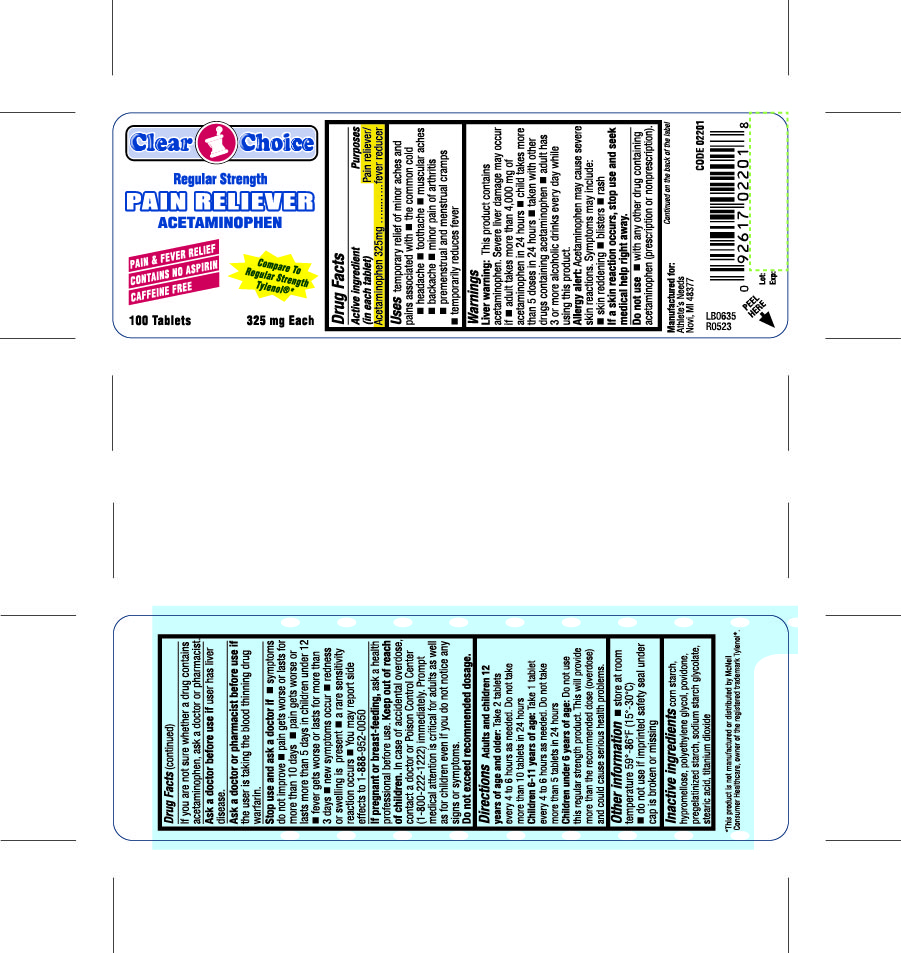 DRUG LABEL: Clear Choice Regular Strength Pain Reliever
NDC: 53185-005 | Form: TABLET
Manufacturer: Athlete's Needs, Inc.
Category: otc | Type: HUMAN OTC DRUG LABEL
Date: 20181211

ACTIVE INGREDIENTS: ACETAMINOPHEN 325 mg/1 1
INACTIVE INGREDIENTS: STARCH, CORN; HYPROMELLOSES; POLYETHYLENE GLYCOL, UNSPECIFIED; STEARIC ACID; TITANIUM DIOXIDE; POVIDONE; SODIUM STARCH GLYCOLATE TYPE A CORN

Clear Choice Regular Strength Pain Reliever

Active Ingredient (in each tablet)

Acetaminophen 325 mg

Purposes

Pain reliever / fever reducer

Uses

temporary relief of minor aches and pains associated with

- the common cold
- headache
- toothache
- muscular aches
- backache
- minor pain of arthritis
- premenstrual and menstrual cramps
- temporarily reduces fever

Warnings

Liver warning: This product contains acetaminophen, Severe liver damage may occur if

- adult takes more than 4,000 mg of acetaminophen in 24 hours
- child takes more than 5 doses in 24 hours
- taken with other drugs containing acetaminophen
- adult has 3 or more alcoholic drinks ever day while using this product

Allergy alert: Acetaminophen may cause sever skin reactions. symptoms may include:

- skin reddening
- blisters
- rash

if a skin reaction occurs, stop use and seek medical help right away.

Do not use

- with any other drug containing acetaminophen (prescription or nonprescription).

If you are not sure whether a drug contains acetaminophen, ask a doctor or pharmacist.

Ask a doctor before use if

user has liver disease

Ask a doctor or pharmacist before use if

the user is taking the blood thinning drug warfarin

Stop use and ask a doctor if

- symptoms do not improve
- pain gets worse or lasts for more than 10 days
- pain gets worse or lasts more than 5 days in children under 12
- fever gets worse or lasts for more than 3 days
- new symptoms occur
- redness or swelling is present
- a rare sensitivity reaction occurs
- You may report side effects to 1-888-952-0050

If pregnant or breast-feeding,

ask a health professional before use.

Keep out of reach of children.

In case of accidental overdose, contact a doctor or Poison Control Center (1-800-222-1222) immediately.

Prompt medical attention is critical for adults as well as children even if you do not notice any signs or symptoms.

Do not exceed recommended dosage.

Directions

Adults and children 12 years of age and older:

Take 2 tablets every 4 to 6 hours as needed.

Do not take more than 10 tablets in 24 hours

Children 6 to 11 years of age: Take 1 tablet every 4 to 6 hours as needed

Do not take more than 5 tablets in 24 hours

Children under 6 years of age:

Do not use this regular strenght product. this will provide more than the recommended dose (overdose) and could cause serious health problems

Other information

- store at room temperature 59º-86ºF (15º-30ºC)
- do not use if imprinted safety seal under cap is broken or missing

Inactive ingredients

corn starch, hypromellose, polyethylene glycol, povidone, pregelatinized starch, sodium starch glycolate, stearic acid, titanium dioxide

Package Label

Clear Choice

Regular Strength

PAIN RELIEVER

ACETAMINOPHEN

PAIN & FEVER RELIEF

CONTAINS NO ASPIRIN

CAFFEINE FREE

Compare to Regular Strength Tylenol (R)

100 Tablets

325 mg Each

Questions?
Contact A.N.I. 6029 Renaissance Place, Toledo OH 43623
Manufactured for A.N.I.

Pain Reliever